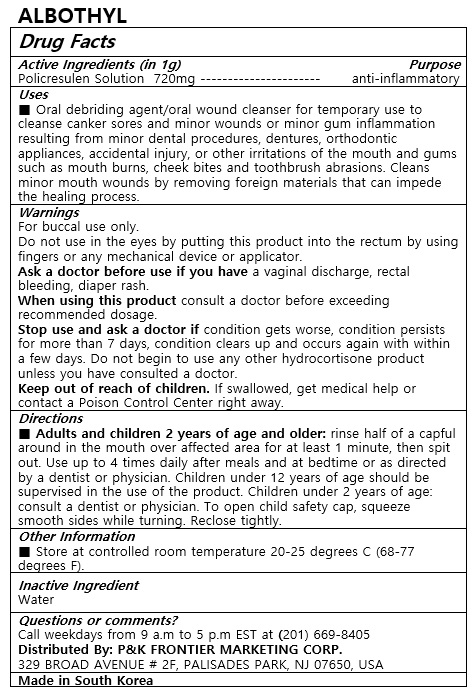 DRUG LABEL: ALBOTHYL
NDC: 72689-0040 | Form: SOLUTION
Manufacturer: OASIS TRADING
Category: otc | Type: HUMAN OTC DRUG LABEL
Date: 20190319

ACTIVE INGREDIENTS: POLICRESULEN 720 mg/1 mL
INACTIVE INGREDIENTS: WATER

ACTIVE INGREDIENT

Policresulen

PURPOSE

Oral debriding agent/oral wound cleanser for temporary use to cleanse canker sores and minor wounds or minor gum inflammation resulting from minor dental procedures, dentures, orthodontic appliances, accidental injury, or other irritations of the mouth and gums such as mouth burns, cheek bites and toothbrush abrasions. Cleans minor mouth wounds by removing foreign materials that can impede the healing process.

Keep out of reach of children

INDICATIONS AND USAGE

Adults and children 2 years of age and older: rinse half of a capful around in the mouth over affected area for at least 1 minute, then spit out. Use up to 4 times daily after meals and at bedtime or as directed by a dentist or physician. Children under 12 years of age should be supervised in the use of the product. Children under 2 years of age: consult a dentist or physician. To open child safety cap, squeeze smooth sides while turning. Reclose tightly.

WARNINGS

For buccal use only.

Do not use in the eyes by putting this product into the rectum by using fingers or any mechanical device or applicator.

Ask a doctor before use if you have a vaginal discharge, rectal bleeding, diaper rash.

When using this product consult a doctor before exceeding recommended dosage.

Stop use and ask a doctor if condition gets worse, condition persists for more than 7 days, condition clears up and occurs again with within a few days. Do not begin to use any other hydrocortisone product unless you have consulted a doctor.

Keep out of reach of children. If swallowed, get medical help or contact a Poison Control Center right away.

INACTIVE INGREDIENT

Water

DOSAGE AND ADMINISTRATION

For buccal use only